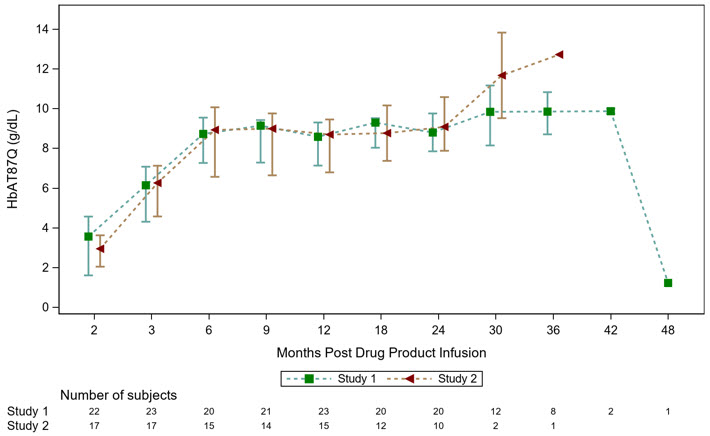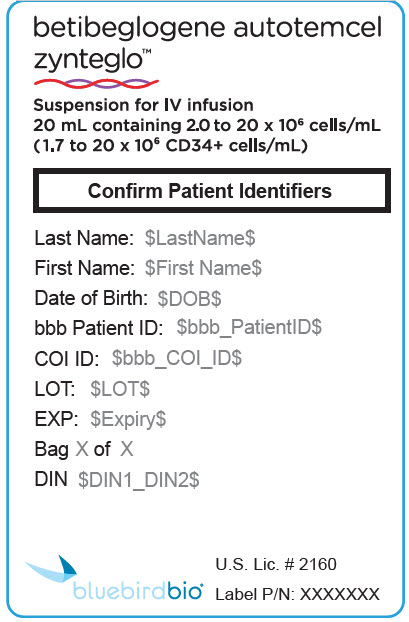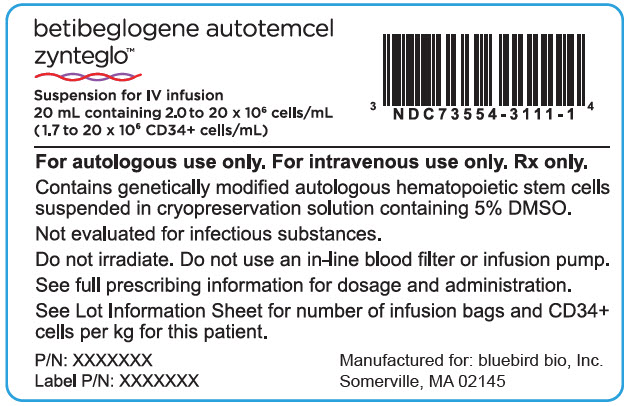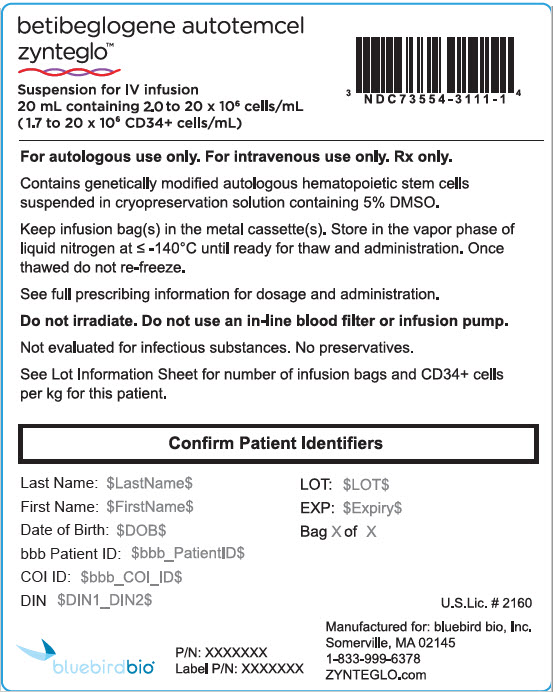 DRUG LABEL: Zynteglo
NDC: 73554-3111 | Form: SUSPENSION
Manufacturer: Genetix Biotherapeutics Inc.
Category: other | Type: CELLULAR THERAPY
Date: 20251223

ACTIVE INGREDIENTS: betibeglogene autotemcel 20000000 1/1 1
INACTIVE INGREDIENTS: CRYOSTOR CS5

HIGHLIGHTS OF PRESCRIBING INFORMATION

These highlights do not include all the information needed to use ZYNTEGLO® safely and effectively. See full prescribing information for ZYNTEGLO.
ZYNTEGLO (betibeglogene autotemcel) suspension for intravenous infusion
Initial U.S. Approval: 2022

1 INDICATIONS AND USAGE

ZYNTEGLO is an autologous hematopoietic stem cell-based gene therapy indicated for the treatment of adult and pediatric patients with β-thalassemia who require regular red blood cell (RBC) transfusions. (1)

2 DOSAGE AND ADMINISTRATION

For autologous use only. For intravenous use only.

- Patients are required to undergo hematopoietic stem cell (HSC) mobilization followed by apheresis to obtain CD34+ cells for ZYNTEGLO manufacturing. (2.2)
- Dosing of ZYNTEGLO is based on the number of CD34+ cells in the infusion bag(s) per kg of body weight. (2.1)
- The minimum recommended dose is 5.0 × 10^6 CD34+ cells/kg. (2.1)
- Full myeloablative conditioning must be administered before infusion of ZYNTEGLO. (2.2)
- Prophylaxis for hepatic veno-occlusive disease (VOD) is recommended. Prophylaxis for seizures should be considered. (2.2)
- Verify that the patient's identity matches the unique patient identification information on the ZYNTEGLO infusion bag(s) prior to infusion. (2.2)
- Do not sample, alter, or irradiate ZYNTEGLO. (2.2)
- Do not use an in-line blood filter or an infusion pump. (2.3)
- Administer each infusion bag of ZYNTEGLO via intravenous infusion over a period of less than 30 minutes. (2.3)

3 DOSAGE FORMS AND STRENGTHS

- ZYNTEGLO is a cell suspension for intravenous infusion. (3)
- A single dose of ZYNTEGLO contains a minimum of 5.0 × 10^6 CD34+ cells/kg of body weight, in one or more infusion bags. (3)

4 CONTRAINDICATIONS

None. (4)

5 WARNINGS AND PRECAUTIONS

- Delayed Platelet Engraftment: Monitor platelet counts until platelet engraftment and recovery are achieved. Patients should be monitored for thrombocytopenia and bleeding. (5.1)
- Risk of Neutrophil Engraftment Failure: Monitor absolute neutrophil counts (ANC) after ZYNTEGLO infusion. If neutrophil engraftment does not occur administer rescue cells. (5.2)
- Risk of Insertional Oncogenesis: Monitor patients at least annually for hematologic malignancies for at least 15 years after ZYNTEGLO infusion. (5.3)
- Hypersensitivity Reactions: Monitor for hypersensitivity reactions during infusion. (5.4)

6 ADVERSE REACTIONS

The most common non-laboratory adverse reactions (incidence ≥ 20%) were mucositis, febrile neutropenia, vomiting, pyrexia (fever), alopecia (hair loss), epistaxis (nose bleed), abdominal pain, musculoskeletal pain, cough, headache, diarrhea, rash, constipation, nausea, decreased appetite, pigmentation disorder, and pruritus (itch). (6.1)

The most common Grade 3 or 4 laboratory abnormalities (> 50%) include neutropenia, thrombocytopenia, leukopenia, anemia, and lymphopenia. (6.1)

To report SUSPECTED ADVERSE REACTIONS, contact bluebird bio at 1-833-999-6378 or FDA at 1-800-FDA-1088 or www.fda.gov/medwatch.

7 DRUG INTERACTIONS

- Anti-retrovirals and Hydroxyurea: Do not take anti-retroviral medications or hydroxyurea for one month prior to mobilization, or for the expected duration for elimination of the medications, and until all cycles of apheresis are completed (7.2)
- Iron Chelation: Discontinue iron chelators 7 days prior to initiation of myeloablative conditioning. Avoid use of myelosuppressive iron chelators for 6 months after ZYNTEGLO infusion. (7.3)

FULL PRESCRIBING INFORMATION

1 INDICATIONS AND USAGE

ZYNTEGLO is indicated for the treatment of adult and pediatric patients with β-thalassemia who require regular red blood cell (RBC) transfusions.

2 DOSAGE AND ADMINISTRATION

For autologous use only. For one-time single-dose intravenous use only.

2.1 Dose

ZYNTEGLO is provided as a single dose for infusion containing a suspension of CD34+ cells in one or more infusion bags. The minimum recommended dose of ZYNTEGLO is 5.0 × 10^6 CD34+ cells/kg.

See the Lot Information Sheet provided with the product shipment for additional information pertaining to dose.

2.2 Preparation Before ZYNTEGLO Infusion

Before mobilization, apheresis, and myeloablative conditioning are initiated, confirm that hematopoietic stem cell (HSC) transplantation is appropriate for the patient.

It is recommended that patients be maintained at a hemoglobin (Hb) ≥ 11 g/dL for at least 30 days prior to mobilization and 30 days prior to myeloablative conditioning.

Granulocyte-colony stimulating factor (G-CSF) and plerixafor were used for mobilization and busulfan was used for myeloablative conditioning. Refer to the prescribing information for the mobilization agent(s) and the myeloablative conditioning agent(s) prior to treatment.

Perform screening for hepatitis B virus (HBV), hepatitis C virus (HCV), human T-lymphotrophic virus 1 & 2 (HTLV-1/HTLV-2), and human immunodeficiency virus 1 & 2 (HIV-1/HIV-2) in accordance with clinical guidelines before collection of cells for manufacturing.

Mobilization and Apheresis

Patients are required to undergo HSC mobilization followed by apheresis to obtain CD34+ cells for product manufacturing.

The target number of CD34+ cells to be collected is ≥ 12 × 10^6 CD34+ cells/kg. If the minimum dose of 5.0 × 10^6 CD34+ cells/kg is not met, the patient may undergo additional cycles of mobilization and apheresis, separated by at least 14 days, in order to obtain more cells for additional manufacture. Up to two drug product lots may be administered to meet the target dose.

A back-up collection of CD34+ cells of ≥ 1.5 × 10^6 CD34+ cells/kg (if collected by apheresis) or > 1.0 × 10^8 TNC/kg (Total Nucleated Cells, if collected by bone marrow harvest) is required. These cells must be collected from the patient and be cryopreserved prior to myeloablative conditioning. The back-up collection may be needed for rescue treatment if there is: 1) compromise of hematopoietic stem cells or ZYNTEGLO before infusion, 2) primary engraftment failure, or 3) loss of engraftment after infusion with ZYNTEGLO.

Myeloablative Conditioning

Full myeloablative conditioning must be administered before infusion of ZYNTEGLO. Consult prescribing information for the myeloablative conditioning agent(s) prior to treatment.

Stop iron chelation at least 7 days prior to myeloablative conditioning. Prophylaxis for hepatic veno-occlusive disease (VOD) is recommended [see Clinical Studies (14)]. Prophylaxis for seizures should be considered, as appropriate.

Do not begin myeloablative conditioning until the complete set of infusion bag(s) constituting the dose of ZYNTEGLO has been received and stored at the treatment center and the availability of the back-up collection is confirmed. After completion of the myeloablative conditioning, allow a minimum of 48 hours of washout before ZYNTEGLO infusion.

Receipt and Storage of ZYNTEGLO

- ZYNTEGLO is shipped to the treatment center in the vapor phase of liquid nitrogen shipper.
- Confirm patient identifiers on the product label(s) and Lot Information Sheet within the shipper.
- If there are any concerns about the product or packaging upon receipt, contact bluebird bio at 1-833-999-6378.
- Keep the infusion bag(s) in the metal cassette(s) and transfer ZYNTEGLO from the vapor phase of liquid nitrogen shipper to the treatment center vapor phase of liquid nitrogen storage at ≤ -140°C (≤ -220°F). Store in the vapor phase of liquid nitrogen at ≤ -140°C (≤ -220°F) until ready for thaw and administration.

Preparation of ZYNTEGLO for Infusion

Coordinate the timing of ZYNTEGLO thaw and infusion. Confirm the infusion time in advance and adjust the start time of ZYNTEGLO thaw such that it will be available for infusion when the patient and healthcare providers are ready.

1. Remove each metal cassette from liquid nitrogen storage and remove each infusion bag from the metal cassette.
2. Confirm that ZYNTEGLO is printed on the infusion bag(s).
3. Confirm that patient identity matches the unique patient identifiers located on the ZYNTEGLO infusion bag(s). Do not infuse ZYNTEGLO if the information on the patient-specific label on the infusion bag does not match the intended patient, and contact bluebird bio at 1-833-999-6378.
4. Ensure the correct number of infusion bags are present. Use the accompanying Lot Information Sheet to confirm that each infusion bag is within the expiration date.
5. Inspect each infusion bag for any breaches of integrity before thawing and infusion. If an infusion bag is compromised, follow the local guidelines and contact bluebird bio immediately at 1-833-999-6378.
6. If more than one infusion bag is provided, thaw and administer each infusion bag completely before proceeding to thaw the next infusion bag.
7. Thaw ZYNTEGLO at 37°C (98.6°F) in a water bath or dry bath. Thawing of each infusion bag takes approximately 2 to 4 minutes. Do not leave ZYNTEGLO unattended. Do not submerge the infusion ports in a water bath.
8. After thaw, mix the contents gently by massaging the infusion bag to disperse clumps of cellular material until all of the contents are uniform. If visible cell clumps remain, continue to gently mix the contents of the bag. Most small clumps of cellular material should disperse with gentle manual mixing. Do not filter, wash, spin down and/or resuspend ZYNTEGLO in new media prior to infusion.
9. Do not sample, alter, irradiate or refreeze ZYNTEGLO.

2.3 Administration

ZYNTEGLO is for autologous use only. The patient's identity must match the patient identifiers on the ZYNTEGLO cassette(s) and infusion bag(s). Do not infuse ZYNTEGLO if the information on the patient-specific label does not match the intended patient.

- Product must be administered within 4 hours after thawing.
- Do not use an in-line blood filter or an infusion pump.

1. Before infusion, confirm that the patient's identity matches the unique patient identifiers on the ZYNTEGLO infusion bag(s). Use the Lot Information Sheet to confirm the total number of infusion bags to be administered.
2. Expose the sterile port on the infusion bag by tearing off the protective wrap covering the port.
3. Access the infusion bag and infuse ZYNTEGLO as soon as possible after thawing and complete the infusion within 4 hours.
4. Administer each infusion bag of ZYNTEGLO via intravenous infusion over a period of less than 30 minutes. If more than one infusion bag is provided, administer each infusion bag completely before proceeding to thaw and infuse the next infusion bag.
5. Flush all ZYNTEGLO remaining in the infusion bag(s) and any associated tubing with at least 50 mL of 0.9% sodium chloride solution to ensure that as many cells as possible are infused into the patient.

After ZYNTEGLO Administration

Standard procedures for patient management after HSC transplantation should be followed after ZYNTEGLO infusion.

- Irradiate any blood products required within the first 3 months after ZYNTEGLO infusion.
- Granulocyte-colony stimulating factor (G-CSF) is not recommended for 21 days after ZYNTEGLO infusion.
- Restarting iron chelation after ZYNTEGLO infusion may be necessary and should be based on clinical practice [see Drug Interactions (7.3) and Clinical Studies (14)]. Phlebotomy can be used in lieu of iron chelation, when appropriate.
- Patients should not donate blood, organs, tissues, or cells at any time in the future.

ZYNTEGLO contains human blood cells that are genetically modified with replication-incompetent, self-inactivating lentiviral vector. Follow universal precautions and biosafety guidelines (Biosafety Level 2) for handling and disposal of ZYNTEGLO to avoid potential transmission of infectious diseases.

3 DOSAGE FORMS AND STRENGTHS

ZYNTEGLO is a cell suspension for intravenous infusion.

ZYNTEGLO is composed of up to four infusion bags which contain 2.0 to 20 × 10^6 cells/mL suspended in cryopreservation solution [see How Supplied/Storage and Handling (16)]. Each infusion bag contains approximately 20 mL of ZYNTEGLO. A single dose of ZYNTEGLO contains a minimum of 5.0 × 10^6 CD34+ cells per kg of body weight, suspended in cryopreservation solution.

See the Lot Information Sheet for actual dose.

4 CONTRAINDICATIONS

None.

5 WARNINGS AND PRECAUTIONS

5.1 Delayed Platelet Engraftment

Delayed platelet engraftment has been observed with ZYNTEGLO treatment. Bleeding risk is increased prior to platelet engraftment and may continue after engraftment in patients with prolonged thrombocytopenia; 15% of patients had ≥ Grade 3 decreased platelets on or after Day 100.

Patients should be made aware of the risk of bleeding until platelet recovery has been achieved. Monitor patients for thrombocytopenia and bleeding according to standard guidelines. Conduct frequent platelet counts until platelet engraftment and platelet recovery are achieved. Perform blood cell count determination and other appropriate testing whenever clinical symptoms suggestive of bleeding arise.

5.2 Risk of Neutrophil Engraftment Failure

There is a potential risk of neutrophil engraftment failure after treatment with ZYNTEGLO. Neutrophil engraftment failure is defined as failure to achieve three consecutive absolute neutrophil counts (ANC) ≥ 500 cells/microliter obtained on different days by Day 43 after infusion of ZYNTEGLO. Monitor neutrophil counts until engraftment has been achieved. If neutrophil engraftment failure occurs in a patient treated with ZYNTEGLO, provide rescue treatment with the back-up collection of CD34+ cells.

5.3 Risk of Insertional Oncogenesis

There is a potential risk of lentiviral vector (LVV)-mediated insertional oncogenesis after treatment with ZYNTEGLO.

Patients treated with ZYNTEGLO may develop hematologic malignancies and should be monitored lifelong. Monitor for hematologic malignancies with a complete blood count (with differential) at Month 6 and Month 12 and then at least annually for at least 15 years after treatment with ZYNTEGLO, and integration site analysis at Months 6, 12, and as warranted.

In the event that a malignancy occurs, contact bluebird bio at 1-833-999-6378 for reporting and to obtain instructions on collection of samples for testing.

5.4 Hypersensitivity Reactions

Allergic reactions may occur with the infusion of ZYNTEGLO. The dimethyl sulfoxide (DMSO) in ZYNTEGLO may cause hypersensitivity reactions, including anaphylaxis.

5.5 Anti-retroviral and Hydroxyurea Use

Patients should not take prophylactic HIV anti-retroviral medications or hydroxyurea for at least one month prior to mobilization, or for the expected duration for elimination of the medications, and until all cycles of apheresis are completed [see Drug Interactions (7.2)].

If a patient requires anti-retrovirals for HIV prophylaxis, then confirm a negative test for HIV before beginning mobilization and apheresis of CD34+ cells.

5.6 Interference with Serology Testing

Patients who have received ZYNTEGLO are likely to test positive by polymerase chain reaction (PCR) assays for HIV due to integrated BB305 LVV proviral DNA, resulting in a false-positive test for HIV. Therefore, patients who have received ZYNTEGLO should not be screened for HIV infection using a PCR-based assay.

6 ADVERSE REACTIONS

The following adverse reactions are described elsewhere in the labeling:

- Delayed Platelet Engraftment [see Warnings and Precautions (5.1)]
- Risk of Neutrophil Engraftment Failure [see Warnings and Precautions (5.2)]
- Risk of Insertional Oncogenesis [see Warnings and Precautions (5.3)]
- Hypersensitivity Reactions [see Warnings and Precautions (5.4)]

6.1 Clinical Trials Experience

Because clinical trials are conducted under widely varying conditions, adverse reaction rates observed in the clinical trials of a drug cannot be directly compared to rates in the clinical trials of another drug and may not reflect the rates observed in practice.

The safety data described in this section reflect exposure to ZYNTEGLO in two open-label, single-arm clinical trials and one long-term follow-up study, in which 41 patients with β-thalassemia requiring regular transfusions were treated with ZYNTEGLO [see Clinical Studies (14)]. The median (min, max) age across the trials was 13 (4, 34) years; 49% were females; 49% were Asian, 44% White, 5% Other, 2% Not Reported. The median (min, max) duration of follow-up was 27.2 (4.1, 48.2) months.

In the two trials, serious adverse reactions occurred in 37% of patients as of last follow-up. The most common serious adverse reactions (> 3%) were pyrexia (fever), thrombocytopenia, liver veno-occlusive disease, febrile neutropenia, neutropenia, and stomatitis. There were no deaths.

The most common adverse reactions (≥ 20%) were mucositis, febrile neutropenia, vomiting, pyrexia (fever), alopecia (hair loss), epistaxis (nose bleed), abdominal pain, musculoskeletal pain, cough, headache, diarrhea, rash, constipation, nausea, decreased appetite, pigmentation disorder, and pruritus (itch).

Table 1 presents the non-laboratory treatment emergent adverse reactions reported in at least 10% of patients and Table 2 describes the laboratory abnormalities of Grade 3 or 4 that occurred in at least 10% of patients.

Table 1: Summary of Non-Laboratory Treatment Emergent Adverse Reactions in at Least 10% of Patients; Day 1 – Month 24 After ZYNTEGLO Administration [Includes adverse events associated with busulfan myeloablative conditioning.] (N = 41)
Adverse Reaction | % Any Grade | % Grade 3 or Higher
Blood and lymphatic system disorders
Febrile neutropenia | 51 | 51
Gastrointestinal disorders
Mucositis [Mucositis includes anal inflammation, mucosal inflammation, oral mucosal exfoliation, oral mucosal roughening, pharyngeal inflammation, stomatitis.] [Encompasses more than one system organ class.] | 95 | 63
Vomiting | 49 | 0
Abdominal pain [Abdominal pain includes abdominal pain, abdominal pain lower, abdominal discomfort, abdominal pain upper.] | 39 | 2
Diarrhea | 27 | 0
Nausea | 24 | 2
Constipation | 24 | 0
Dyspepsia | 10 | 5
Gingival bleeding | 10 | 2
General disorders and administration site conditions
Pyrexia | 49 | 12
Fatigue | 12 | 0
Hepatobiliary disorders
Venoocclusive liver disease | 10 | 7
Infections and infestations
Viral infection [Viral infection includes BK virus infection, human rhinovirus test positive, influenza, influenza like illness, parainfluenza virus infection, rhinovirus infection, SARS-CoV-2 test positive, viral infection.] | 17 | 2
Upper respiratory tract infections [Upper respiratory tract infections include upper airway cough syndrome, upper respiratory tract infection, viral upper respiratory tract infection, pharyngitis, pharyngitis streptococcal.] | 15 | 0
Nasopharyngitis | 12 | 0
Sepsis [Sepsis includes bacterial sepsis, neutropenic sepsis, fungal sepsis, sepsis.] | 10 | 10
Injury, poisoning and procedural complications
Procedural pain | 15 | 0
Transfusion reaction | 15 | 0
Metabolism and nutrition disorders
Decreased appetite | 24 | 15
Musculoskeletal and connective tissue disorders
Musculoskeletal pain [Musculoskeletal pain includes musculoskeletal pain, musculoskeletal chest pain, bone pain, musculoskeletal discomfort, chest pain, myalgia, neck pain, non-cardiac chest pain, pain in extremity, spinal pain, tendon pain, back pain.] | 37 | 0
Nervous system disorders
Headache [Headache includes headache, migraine.] | 29 | 0
Respiratory, thoracic and mediastinal disorders
Epistaxis | 42 | 20
Cough [Cough includes cough, upper-airway cough syndrome, productive cough.] | 34 | 0
Oropharyngeal pain [Oropharyngeal pain includes oropharyngeal pain, oral pain, oropharyngeal discomfort, jaw pain.] | 15 | 0
Dyspnea | 12 | 0
Hypoxia | 12 | 7
Rhinitis [Rhinitis includes rhinitis, rhinorrhea, rhinitis allergic.] | 12 | 0
Skin and subcutaneous tissue disorders
Alopecia | 44 | 0
Rash [Rash includes acne, dermatitis acneiform, dermatitis atopic, macule, petechiae, rash, rash follicular, rash macular, rash maculo-papular, rash pruritic, rash pustular, rash vesicular.] | 27 | 0
Pigmentation disorder [Pigmentation disorder includes oral pigmentation, pigmentation disorder, skin hyperpigmentation, skin hypopigmentation.] | 24 | 0
Pruritus | 22 | 0
Vascular disorders
Hypertension | 10 | 0

Other clinically important adverse reactions that occurred in less than 10% of patients include the following:

Cardiac disorders: congestive heart failure (2%)

Hepatobiliary disorders: Serious hepatic veno-occlusive disease (VOD) occurred in 3 (7%) patients; of these three, two had not received prophylaxis for VOD. All patients who experienced serious VOD received treatment with defibrotide and recovered. Patients with β-thalassemia requiring regular transfusions may be at an increased risk of VOD following myeloablative conditioning.^1

Infections and infestations: pneumonia (7%)

Infusion-related reaction including abdominal pain (7%) and tachycardia (2%).

Table 2: Grade 3 or 4 Treatment Emergent Laboratory Abnormalities Occurring in ≥ 10% of Patients Following Treatment with ZYNTEGLO [Includes lab abnormalities associated with busulfan myeloablative conditioning.] from Day 1 to Month 24 (N = 41) [The denominator is 36 for hyperglycemia, due to missing data.]
Laboratory Abnormality [Baseline lab values were assessed prior to apheresis.] | Grade 3 or 4 (%)
Neutropenia | 100
Thrombocytopenia | 100
Leukopenia | 100
Anemia | 95
Lymphopenia | 61
ALT Increased | 24
Hypophosphatemia | 20
Hyperglycemia | 14
Hypokalemia | 12
Hyperbilirubinemia | 10
Hyponatremia | 10
Abbreviations: ALT: alanine aminotransferase

Platelet Engraftment Delay

Platelet engraftment was defined as three consecutive platelet values ≥ 20,000 cells/microliter, obtained on different days after ZYNTEGLO infusion, with no platelet transfusions administered for 7 days immediately preceding and during the evaluation period. Forty-one patients treated with ZYNTEGLO achieved platelet engraftment by a median of Day 46 (range 20 - 94) in clinical studies. Patients without a spleen reached the criterion for platelet engraftment earlier as compared to patients with an intact spleen: median Day 42 (range, 21 - 53 days) vs. median Day 50 (range, 20 - 94 days), respectively. Patients achieving platelet engraftment at ≥ Day 46 did not have an increased incidence of bleeding compared with patients with platelet engraftment at < Day 46.

Neutrophil Engraftment

While all subjects achieved neutrophil engraftment after ZYNTEGLO in the clinical studies, 7% of patients remained dependent on G-CSF beyond Day 43, one through Day 77. G-CSF discontinuation was followed by transient decreases in neutrophil counts to < 500 cells/microliter after Day 43 in six (15%) patients.

7 DRUG INTERACTIONS

No formal drug interaction studies have been performed. ZYNTEGLO is not expected to interact with the hepatic cytochrome P-450 family of enzymes or drug transporters.

7.1 Live Vaccines

Follow institutional guidelines for vaccine administration. The safety of immunization with live viral vaccines during or following ZYNTEGLO treatment has not been studied.

7.2 Anti-retrovirals and Hydroxyurea

Patients should not take anti-retroviral medications or hydroxyurea for at least one month prior to mobilization or the expected duration for elimination of the medications, and until all cycles of apheresis are completed [see Warnings and Precautions (5.5)]. Anti-retroviral medications may interfere with manufacturing of the apheresed cells.

7.3 Iron Chelation

Drug-drug interactions between iron chelators and the myeloablative conditioning agent must be considered. Iron chelators should be discontinued at least 7 days prior to initiation of conditioning. The prescribing information for the iron chelator(s) and the myeloablative conditioning agent should be consulted for the recommendations regarding co-administration with CYP3A substrates.

Some iron chelators are myelosuppressive. After ZYNTEGLO infusion, avoid use of these iron chelators for 6 months. If iron chelation is needed, consider administration of non-myelosuppressive iron chelators. Phlebotomy can be used in lieu of iron chelation, when appropriate [see Clinical Studies (14)].

7.4 Erythropoiesis-Stimulating Agents

There is no clinical experience with the use of erythropoiesis-stimulating agents in patients treated with ZYNTEGLO.

8 USE IN SPECIFIC POPULATIONS

8.1 Pregnancy

Risk Summary

There are no available data with ZYNTEGLO administration in pregnant women. Consider the risks associated with myeloablative conditioning agents on pregnancy and fertility.

No reproductive and developmental toxicity studies in animals have been conducted with ZYNTEGLO to assess whether it can cause fetal harm when administered to a pregnant woman. It is not known whether ZYNTEGLO has the potential to be transferred to the fetus. Therefore, ZYNTEGLO should not be administered to women who are pregnant, and pregnancy after ZYNTEGLO infusion should be discussed with the treating physician.

No nonclinical germline transmission studies have been conducted with ZYNTEGLO.

In the U.S. general population, the estimated background risk of major birth defects and miscarriage in clinically recognized pregnancies is 2-4% and 15-20%, respectively.

8.2 Lactation

Risk Summary

There is no information regarding the presence of ZYNTEGLO in human milk, the effect on the breastfed infant, and the effects on milk production. The developmental and health benefits of breastfeeding should be considered along with the mother's clinical need for ZYNTEGLO and any potential adverse effects on the breastfed child from ZYNTEGLO. Therefore, ZYNTEGLO is not recommended for women who are breastfeeding, and breastfeeding after ZYNTEGLO infusion should be discussed with the treating physician.

8.3 Females and Males of Reproductive Potential

Pregnancy Testing

A negative serum pregnancy test must be confirmed prior to the start of mobilization and re-confirmed prior to conditioning procedures and before ZYNTEGLO administration.

Contraception

There are insufficient exposure data to provide a precise recommendation on duration of contraception following treatment with ZYNTEGLO.

Women of childbearing potential and men capable of fathering a child should use an effective method of contraception (intra-uterine device or combination of hormonal and barrier contraception) from start of mobilization through at least 6 months after administration of ZYNTEGLO. Advise patients of the risks associated with conditioning agents.

Infertility

There are no data on the effects of ZYNTEGLO on fertility.

Data are available on the risk of infertility with myeloablative conditioning. Advise patients of the option to cryopreserve semen or ova before treatment, if appropriate.

8.4 Pediatric Use

The safety and efficacy of ZYNTEGLO have been established in pediatric patients with β-thalassemia requiring regular transfusions. Use of ZYNTEGLO is supported by two Phase 3 studies [see Clinical Studies (14)] that included 27 pediatric patients in the following age groups: 16 children (less than 12 years) and 11 adolescents (age 12 years to less than 18 years).

No differences in efficacy or clinical safety were observed between the adult and pediatric subgroups. Engraftment times were longer in pediatric patients, but not associated with increases in infections or bleeding events. The median (min, max) time to neutrophil engraftment for patients less than 18 years was 26 (16, 39) days versus 21 (13, 27) days for patients 18 years or older. The median (min, max) time to platelet engraftment for patients less than 18 years was 50 (20, 94) days versus 43 (21, 58) days for patients 18 years or older. Longer engraftment time was associated with intact spleens.

The safety and efficacy of ZYNTEGLO in children less than 4 years of age have not been established. No data are available.

8.5 Geriatric Use

ZYNTEGLO has not been studied in patients > 65 years of age. Hematopoietic stem cell (HSC) transplantation must be appropriate for a patient to be treated with ZYNTEGLO.

8.6 Patients Seropositive for Human Immunodeficiency Virus (HIV)

ZYNTEGLO has not been studied in patients with HIV-1, HIV-2, HTLV-1, or HTLV-2. A negative serology test for HIV is necessary to ensure acceptance of apheresis material for ZYNTEGLO manufacturing. Apheresis material from patients with a positive test for HIV will not be accepted for ZYNTEGLO manufacturing.

8.7 Renal Impairment

ZYNTEGLO has not been studied in patients with renal impairment. Patients should be assessed for renal impairment, defined as creatinine clearance ≤ 70 mL/min/1.73 m^2, to ensure HSC transplantation is appropriate.

8.8 Hepatic Impairment

ZYNTEGLO has not been studied in patients with hepatic impairment. Patients should be assessed for hepatic impairment to ensure HSC transplantation is appropriate.

11 DESCRIPTION

ZYNTEGLO (betibeglogene autotemcel) is a βA-T87Q-globin gene therapy consisting of autologous CD34+ cells, containing hematopoietic stem cells (HSCs), transduced with BB305 LVV encoding βA-T87Q-globin, suspended in cryopreservation solution. ZYNTEGLO is intended for one-time administration to add functional copies of a modified form of the β-globin gene (βA-T87Q-globin gene) into the patient's own HSCs.

ZYNTEGLO is prepared from the patient's own HSCs, which are collected via apheresis procedure(s). The autologous cells are enriched for CD34+ cells, then transduced ex vivo with BB305 LVV, a self-inactivating LVV. The promoter, a regulatory element of the LVV that controls the expression of the transgene selected for BB305 LVV, is a cellular (non-viral) promoter that controls gene expression specific to the erythroid lineage cells (red blood cells and their precursors). BB305 LVV encodes βA-T87Q-globin. The transduced CD34+ cells are washed, formulated into a suspension, and then cryopreserved. ZYNTEGLO is frozen in a patient-specific infusion bag(s) and is thawed prior to administration [see Dosage and Administration (2.2), How Supplied/Storage and Handling (16)]. The thawed product is colorless to white to red, including shades of white or pink, light yellow, and orange, and may contain small proteinaceous particles. Due to the presence of cells, the solution may be clear to slightly cloudy and may contain visible cell aggregates.

The formulation contains 5% dimethyl sulfoxide (DMSO).

12 CLINICAL PHARMACOLOGY

12.1 Mechanism of Action

ZYNTEGLO adds functional copies of a modified β-globin gene into patients' hematopoietic stem cells (HSCs) through transduction of autologous CD34+ cells with BB305 LVV. After ZYNTEGLO infusion, transduced CD34+ HSCs engraft in the bone marrow and differentiate to produce RBCs containing biologically active βA-T87Q-globin (a modified β-globin protein) that will combine with α-globin to produce functional adult Hb containing βA-T87Q-globin (HbAT87Q). βA-T87Q-globin can be quantified relative to other globin species in peripheral blood using high-performance liquid chromatography. βA-T87Q-globin expression is designed to correct the β/α-globin imbalance in erythroid cells of patients with β-thalassemia and has the potential to increase functional adult HbA and total Hb to normal levels and eliminate dependence on regular pRBC transfusions.

12.2 Pharmacodynamics

HbAT87Q generally increased steadily after ZYNTEGLO infusion and stabilized by approximately Month 6 after infusion (Figure 1). Patients had a Month 6 median (min, max) HbAT87Q of 8.7 (0.0, 12.0) g/dL in the ongoing Phase 3 studies, Study 1 and Study 2 (N = 35).

HbAT87Q remained durable with a median (min, max) of 8.8 (0.3, 12.4) g/dL at Month 24 in the ongoing Phase 3 studies (N = 30). HbAT87Q in the Phase 3 studies continued to remain durable at last follow-up through Month 36, demonstrating sustained expression of the βA-T87Q protein derived from irreversible integration of the βA-T87Q-globin gene into long-term hematopoietic stem cells (HSCs).

Figure 1: Median of HbAT87Q Over Time [Bars represent interquartile ranges] , [Only one patient in Study 1 had HbAT87Q data at Month 48; this patient did not achieve TI, which accounts for the drop in median HbAT87Q for Study 1 at Month 48]

12.3 Pharmacokinetics

ZYNTEGLO is an autologous gene therapy which includes hematopoietic stem cells (HSCs) that have been genetically modified ex vivo. The nature of ZYNTEGLO is such that conventional studies on pharmacokinetics, absorption, distribution, metabolism, and elimination are not applicable.

13 NONCLINICAL TOXICOLOGY

13.1 Carcinogenesis, Mutagenesis, Impairment of Fertility

No carcinogenicity studies have been performed with ZYNTEGLO. Intravenous administration of ZYNTEGLO in a mouse model of β-thalassemia showed no evidence of toxicity, genotoxicity, or oncogenesis (tumorigenicity).

No studies have been conducted to evaluate the effects of ZYNTEGLO on fertility.

14 CLINICAL STUDIES

The efficacy of ZYNTEGLO was evaluated in 2 ongoing Phase 3 open-label, single-arm, 24-month, multicenter studies (Study 1 and Study 2) in 41 patients aged 4 to 34 years with β-thalassemia requiring regular transfusions. Following completion of the 24-month parent studies, patients were invited to enroll in an ongoing long-term safety and efficacy follow-up study for an additional 13 years (Study 3).

Patients were considered to be eligible for the Phase 3 studies if they had a history of transfusions of at least 100 mL/kg/year of packed red blood cells (pRBCs) or with 8 or more transfusions of pRBCs per year in the 2 years preceding enrollment. Table 3 includes the demographics and characteristics for patients in the Phase 3 studies.

Table 3: Demographics and Characteristics for Patients Treated with ZYNTEGLO in Phase 3 Studies
 | Study 1 N = 23 | Study 2 N = 18
Genotype | non-β^0/β^0 | β^0/β^0 or non-β^0/β^0 (12 β^0/β^0; 6 non-β^0/β^0)
Age, years Median (min, max) | 15 (4, 34) | 13 (4, 33)
Sex | 52% females; 48% males | 44% females: 56% males
Race
Asian | 57% | 39%
White | 35% | 56%
Other/Not Reported | 9% | 6%
Baseline [Baseline annualized based on data 2 years prior to enrollment.] transfusion volume, mL/kg/year Median (min, max) | 208 (142, 274) | 194 (75, 289)
Baseline transfusion frequency, transfusions per year Median (min, max) | 16 (12, 37) | 17 (11, 40)
Lansky or Karnofsky Performance Score All patients, minimum score Percentage of patients with score of 100 | ≥ 80 52% | ≥ 90 56%
Cardiac T2* at baseline, msec Median (min, max) | 37 (21, 57) | 37 (15, 75)
Serum Ferritin at baseline, pmol/L Median (min, max) | 4438 (784, 22517) | 3275 (1279, 8874)
Liver Iron concentration at baseline, mg/g Median (min, max) | 5.3 (1.0, 41.0) | 3.6 (1.2, 13.2)

Patients who had severely elevated iron in the heart (i.e., patients with cardiac T2* less than 10 msec by magnetic resonance imaging [MRI]) or advanced liver disease were not accepted into the studies. MRI of the liver was performed on all patients. Patients older than 18 years with MRI results demonstrating liver iron content ≥ 15 mg/g underwent liver biopsy for further evaluation. Patients younger than 18 years with MRI results demonstrating liver iron content ≥ 15 mg/g were excluded from the studies unless a liver biopsy (at the discretion of the investigator) could provide additional data to confirm eligibility. Patients with a liver biopsy demonstrating bridging fibrosis, cirrhosis, or active hepatitis, were also excluded.

Mobilization and Apheresis

All patients were administered G-CSF and plerixafor to mobilize stem cells prior to the apheresis procedure. The planned dose of G-CSF was 10 µg/kg/day in patients with a spleen, and 5 µg/kg/day in patients without a spleen, given in the morning on Days 1 through 5 of mobilization. The planned dose of plerixafor was 0.24 mg/kg/day, given in the evening on Days 4 and 5 of mobilization. Apheresis generally occurred on mobilization Day 5 and 6 and if a third day of collection was needed, plerixafor and G-CSF dosing was extended to Day 6. The dose of G-CSF was decreased by half if the white blood cell (WBC) count exceeded 100 × 10^9/L prior to the day of apheresis. Most patients collected the minimum number of CD34+ cells to manufacture ZYNTEGLO with 1 cycle of mobilization and apheresis.

Pre-treatment Conditioning

All patients received full myeloablative conditioning with busulfan prior to treatment with ZYNTEGLO. The planned dose of busulfan was 3.2 mg/kg/day for patients 18 years and older as a 3-hour IV infusion daily for 4 consecutive days with a recommended target AUC0-24h of 3800-4500 µM*min. The planned dose of busulfan was 0.8 mg/kg for patients younger than 18 years of age as a 2-hour IV infusion every 6 hours for a total of 16 doses with a recommended target of AUC0-6h of 950-1125 µM*min.

The busulfan prescribing information was used for information on the appropriate method for determination of patient weight-based dosing. Busulfan dose adjustments were made as needed based on pharmacokinetic monitoring. In the clinical studies after completion of the 4-day course of busulfan, a washout period of at least 48 hours was required before ZYNTEGLO administration. Busulfan levels were measured 48 hours after final dose of busulfan for retrospective confirmation of adequate washout.

All patients received anti-seizure prophylaxis with agents other than phenytoin prior to initiating busulfan. Phenytoin was not used for anti-seizure prophylaxis because of its induction of cytochrome P450 and resultant increased clearance of busulfan.

Prophylaxis for hepatic veno-occlusive disease (VOD)/hepatic sinusoidal obstruction syndrome was required with ursodeoxycholic acid or defibrotide, per institutional guidelines.

ZYNTEGLO Administration

All patients (N = 41) were administered ZYNTEGLO with a median (min, max) dose of 9.4 (5.0, 42.1) × 10^6 CD34+ cells/kg as an intravenous infusion.

After ZYNTEGLO Administration

G-CSF was not recommended for 21 days after ZYNTEGLO infusion in Phase 3 studies. A total of 24% of patients (N = 10/41) received G-CSF within 21 days after ZYNTEGLO infusion.

Neutrophil engraftment was reported on median (min, max) Day 26 (13, 39) after ZYNTEGLO infusion.

As ZYNTEGLO is an autologous therapy, long-term immunosuppressive agents were not required in clinical studies.

Study 1

Study 1 (NCT02906202) is an ongoing Phase 3 open-label, single-arm, 24-month study to evaluate the efficacy of ZYNTEGLO in 23 patients with β-thalassemia requiring regular transfusions and with a non-β^0/β^0 genotype. Nineteen out of 23 patients have rolled over into a long-term follow-up study (Study 3, NCT02633943) after Month 24.

The median (min, max) duration of follow-up is 29.5 (13.0, 48.2) months. All patients remain alive at last follow-up. There were no cases of graft versus-host disease (GVHD), graft failure, or graft rejection in the clinical studies.

The benefit of ZYNTEGLO was established based on achievement of transfusion independence (TI), defined as a weighted average Hb ≥ 9 g/dL without any pRBC transfusions for a continuous period of ≥ 12 months at any time during the study, after infusion of ZYNTEGLO. Of 22 patients evaluable for TI, 20 (91%, 95% CI: 71, 99) achieved TI with a median (min, max) weighted average Hb during TI of 11.8 (9.7, 13.0) g/dL. All patients who achieved TI maintained TI, with a min, max duration of ongoing TI of 15.7+, 39.4+ months (N = 20) (Table 4). The median (min, max) time to last pRBC transfusion prior to TI was 0.9 (0.5, 2.4) months following ZYNTEGLO infusion. For the patients who were evaluable for TI and did not achieve TI (N = 2), a reduction of 32% and 31% in transfusion volume requirements and a reduction of 30% and 26% in transfusion frequency were observed from 6 months post-drug product infusion to last follow-up compared to pre-enrollment requirements.

After ZYNTEGLO infusion, patient iron removal therapy was managed at physician discretion. Thirteen of the 20 patients who achieved TI are not on chelation therapy as of last follow-up. Of these, 9 (9/13 = 69%) patients did not restart chelation. Four patients (4/13 = 31%) restarted and then stopped iron chelation with a median time from last iron chelation use to last follow-up of 22.7 (7.1, 23.4) months. Of the 20 patients who achieved TI, 7 patients (35%) received phlebotomy to remove iron.

Study 2

Study 2 (NCT03207009) is an ongoing Phase 3 open-label, single-arm, 24-month study to evaluate the efficacy of ZYNTEGLO in 18 patients with β-thalassemia requiring regular transfusions and a β^0/β^0 or non-β^0/β^0 (IVS-I-110/IVS-I-110 or IVS-I-110/ β^0) genotype. Ten out of 18 patients have rolled over into a long-term follow-up study (Study 3, NCT02633943) after Month 24.

The median (min, max) duration of follow-up is 24.6 (4.1, 35.5) months. All patients remain alive at last follow-up. There were no cases of graft-versus-host disease (GVHD), graft failure, or graft rejection in the clinical study.

The efficacy of ZYNTEGLO was established based on achievement of transfusion independence (TI), which is defined as a weighted average Hb ≥ 9 g/dL without any pRBC transfusions for a continuous period of ≥ 12 months at any time during the study, after infusion of ZYNTEGLO. Fourteen patients are evaluable for TI. Of these, 12/14 (86%, 95% CI: 57, 98) achieved TI with a median (min, max) weighted average Hb during TI of 10.20 (9.3, 13.7) g/dL. All patients who achieved TI maintained TI, with a min, max duration of ongoing TI of 12.5+, 32.8+ months (N = 12) (Table 4). The median (min, max) time to last pRBC transfusion prior to TI was 0.8 (0.0, 1.9) months following ZYNTEGLO infusion. For the patients who were evaluable for TI and did not achieve TI (N = 2), a reduction of 92% and 3% in transfusion volume requirements and a reduction of 87% and 21% in transfusion frequency were observed from 6 months post-drug product infusion to last follow-up compared to pre-enrollment requirements.

After ZYNTEGLO infusion, patient iron removal therapy was managed at physician discretion. Seven of the 12 patients who achieved TI are not on chelation therapy as of last follow-up. Of these, three (3/7 = 43%) patients did not restart chelation. Four patients (4/7 = 57%) restarted and then stopped iron chelation with a median time from last iron chelation use to last follow-up of 7.2 (6.0, 21.4) months. Of the 12 patients who achieved TI, one (8%) received phlebotomy to remove iron.

Table 4: Efficacy and Pharmacodynamic Outcomes for Patients Treated with ZYNTEGLO who Achieved Transfusion Independence
 | Study 1 [Includes duration of follow-up from Study 3.] | Study 2 | Overall Results
 | (N = 23) | (N = 18) | (N = 41)
Transfusion Independence (TI) [Transfusion independence (TI): a weighted average Hb ≥ 9 g/dL without any pRBC transfusions for a continuous period of ≥ 12 months at any time during the study after ZYNTEGLO infusion.]
n/N [N represents the total number of patients evaluable for TI, defined as patients who have completed their parent study (i.e., Month 24), or achieved TI, or will not achieve TI in their parent study.] (%) | 20/22 (91%) | 12/14 (86%) | 32/36 (89%)
[95% CI] | [77, 99] | [57, 98] | [74, 97]
Weighted Average Total Hb during TI (g/dL)
n | 20 | 12 | 32
median | 11.8 | 10.2 | 11.5
(min, max) | (9.7, 13.0) | (9.3, 13.7) | (9.3, 13.7)
Duration of TI (months) [Based on Kaplan-Meier.]
n | 20 | 12 | 32
median | NR | NR | NR
(min, max) | (15.7+, 39.4+) | (12.5+, 32.8+) | (12.5+, 39.4+)
HbAT87Q (g/dL) at Month 6
n | 18 | 11 | 29
median | 8.9 | 8.9 | 8.9
(min, max) | (5.2, 10.6) | (3.8, 12.0) | (3.8, 12.0)
HbAT87Q (g/dL) at Month 24
n | 18 | 8 | 26
median | 8.9 | 9.8 | 9.1
(min, max) | (5.0, 11.4) | (7.9, 12.4) | (5.0, 12.4)
Hb [Hb levels are summarized for patients who do not have pRBC transfusions in the prior 60 days.] (g/dL) at Month 6
n | 20 | 12 | 32
median | 11.7 | 10.2 | 11.4
(min, max) | (9.3, 13.3) | (8.8, 13.2) | (8.8, 13.3)
Hb (g/dL) at Month 24
n | 17 | 9 | 27
median | 12.5 | 10.9 | 11.9
(min, max) | (9.5, 13.3) | (9.7, 14.0) | (9.5, 14.0)
NR = Not reached. Hb = Total Hb.

Total Unsupported Hemoglobin Across Studies

All 32 patients in the Phase 3 studies who achieved TI with ZYNTEGLO maintained TI. These patients exhibited durable normal or near-normal total hemoglobin levels with a median (min, max) unsupported total Hb of 11.4 (9.5, 14.8) g/dL at last follow-up.

15 REFERENCES

^1 Lai, X., Liu, L., Zhang, Z. et al. Hepatic veno-occlusive disease/sinusoidal obstruction syndrome after hematopoietic stem cell transplantation for thalassemia major: incidence, management, and outcome. Bone Marrow Transplant 56, 1635–1641 (2021).

16 HOW SUPPLIED/STORAGE AND HANDLING

ZYNTEGLO is supplied in up to four infusion bags containing a frozen suspension of genetically modified autologous cells, enriched for CD34+ cells. Each bag contains approximately 20 mL. Each infusion bag is individually packed within an overwrap in a metal cassette. ZYNTEGLO is shipped from the manufacturing facility to the treatment center storage facility in a cryoshipper, which may contain multiple metal cassettes intended for a single patient. A Lot Information Sheet is affixed inside the shipper.

- 20 mL infusion bag, overwrap, and metal cassette (NDC 73554-3111-1)

STORAGE AND HANDLING

Match the identity of the patient with the patient identifiers on the metal cassette(s), infusion bag(s), and Lot Information Sheet upon receipt.

- Keep the infusion bag(s) in the metal cassette(s) and store in the vapor phase of liquid nitrogen at less than or equal to -140°C (≤ -220°F) until ready for thaw and administration.
- Thaw ZYNTEGLO prior to infusion [see Dosage and Administration (2.2)].
- Do not re-freeze after thawing.
- Do not irradiate ZYNTEGLO, as this could lead to inactivation.

17 PATIENT COUNSELING INFORMATION

Advise the patient to read the FDA-approved patient labeling (Patient Information).

Ensure that patients understand the risk of manufacturing failure. In case of manufacturing failure or the need for additional cells, additional cell collection and manufacturing of ZYNTEGLO would be needed [see Dosage and Administration (2.2)].

Prior to treatment, advise patients of the following:

- Risks associated with mobilization and myeloablative conditioning agents [see Dosage and Administration (2.2), Use in Specific Populations (8.1, 8.3)].
- Delayed platelet engraftment – A risk of bleeding exists after myeloablative conditioning and before platelet engraftment and may continue after engraftment in patients who have continued thrombocytopenia [see Warnings and Precautions (5.1)].
- Risk of neutrophil engraftment failure –Patients who experience neutrophil engraftment failure will receive rescue treatment with their back-up collection of CD34+ cells [see Warnings and Precautions (5.2)].
- Risk of insertional oncogenesis – There is a potential risk of insertional oncogenesis after treatment with ZYNTEGLO. Patients should be monitored lifelong. Monitoring will include assessment for hematologic malignancies with a complete blood count at Month 6 and Month 12 and then at least annually for at least 15 years after treatment with ZYNTEGLO. This will include integration site analysis at Months 6, 12, and as warranted [see Warnings and Precautions (5.3)].

Advise patients to seek immediate attention for the following:

- New or worsening bleeding or bruising. Platelet recovery following ZYNTEGLO infusion could be delayed, potentially resulting in an increased risk of bruising or bleeding until platelet recovery has been achieved [see Warnings and Precautions (5.1), Adverse Reactions (6.1)].

Advise patients to:

- Monitor for signs and symptoms of bleeding and have frequent blood draws for platelet counts, until platelet recovery has been achieved [see Warnings and Precautions (5.1)].
- Have their treating physician contact bluebird bio at 1-833-999-6378 if they are diagnosed with a malignancy [see Warnings and Precautions (5.3)].

Advise patients that they should not donate blood, organs, tissues, or cells at any time in the future [see Dosage and Administration (2.3)].

Advise patients that they may test positive for HIV if tested using a PCR assay after being treated with ZYNTEGLO [see Warnings and Precautions (5.6)].

Manufactured for:
bluebird bio, Inc.
Somerville, MA 02145
US License No 2160

PATIENT INFORMATION
ZYNTEGLO® (pronounced zin-TEH-glo)
(betibeglogene autotemcel)

What is the most important information I should know about ZYNTEGLO?
ZYNTEGLO may cause the following side effects:

- On the day of treatment with ZYNTEGLO
  - Increased heart rate
  - Abdominal pain
- Following treatment for up to 6 months
  - Low level of platelets, which may reduce the ability of blood to clot and may cause bleeding
  - Low level of white blood cells, which may make you more susceptible to infection
  - Pain in arms or legs

Call your healthcare provider right away if you have new or unusual bleeding which may include any of these signs or symptoms:

- Severe headache
- Abnormal bruising
- Nose bleed
- Blood in your urine, stool, or vomit
- Coughing up blood
- Unusual stomach or back pain

You may experience side effects associated with other medicines administered as part of the ZYNTEGLO treatment regimen. Talk to your physician regarding those possible side effects. Your healthcare providers may give you other medicines to treat your side effects.
It is important for you to be monitored at least yearly for at least 15 years for any changes to your blood. There is a potential risk of blood cancer associated with this treatment; however, no cases have been seen in studies of ZYNTEGLO. If you are diagnosed with a cancer, have your treating physician contact bluebird bio at 1-833-999-6378.

What is ZYNTEGLO?
ZYNTEGLO is a one-time gene therapy to treat beta-thalassemia (also known as beta-thalassemia major or Cooley's Anemia) in patients who require regular transfusions. Beta-thalassemia is caused by a change in the beta-globin gene, which causes the body to produce reduced or no beta-globin. ZYNTEGLO is made specifically for each patient, using the patient's own blood stem cells and adds functional copies of the beta-globin gene to your cells. This may allow you to produce sufficient hemoglobin to stop receiving regular transfusions.

How will I get ZYNTEGLO?
Your healthcare providers will give you other medicines, including chemotherapy medicine, as part of your treatment with ZYNTEGLO. It's important to talk to your healthcare provider about the risks and benefits of all medicines involved in your treatment.
After receiving the chemotherapy, it may not be possible for you to become pregnant or father a child. You should consider discussing options for fertility preservation with your doctor before treatment.
STEP 1: ZYNTEGLO is made specifically for you from your own blood stem cells. Your healthcare provider will collect your blood stem cells though a process called mobilization and apheresis (A-feh-REE-sis). This process takes approximately one week and may need to be repeated.
'Back-up' stem cells (or 'rescue cells') are also collected and stored at the hospital. This is a precaution in case there is a problem in the treatment process. If this happens, your back-up stem cells will be given back to you. If you receive back-up cells, you will have no benefit from ZYNTEGLO.
STEP 2: Your blood stem cells will be sent to a manufacturing site where they are used to make ZYNTEGLO. It takes approximately 70-90 days from the time your cells are collected to manufacture and test ZYNTEGLO before it is shipped to your healthcare provider, but the time may vary.
STEP 3: Before you receive ZYNTEGLO, your healthcare provider will give you chemotherapy for a few days to make room in the bone marrow. You will be admitted to the hospital for this step and remain in the hospital until after ZYNTEGLO infusion.
STEP 4: ZYNTEGLO is given by an intravenous infusion (into your vein). You may receive more than one bag of ZYNTEGLO. Each bag is infused in 30 minutes or less.
After ZYNTEGLO infusion, you will stay in the hospital for approximately 3-6 weeks so that your healthcare team can closely monitor your recovery. Your healthcare provider will determine when you can go home.

What should I avoid after receiving ZYNTEGLO?

- Do not donate blood, organs, tissues or cells.

What are the possible or reasonably likely side effects of ZYNTEGLO?
The most common side effects of ZYNTEGLO are:

- On the day of treatment with ZYNTEGLO
  - Increased heart rate
  - Abdominal pain
- Following treatment for up to 6 months
  - Low level of platelets, which may reduce the ability of blood to clot and may cause bleeding
  - Low level of white blood cells, which may make you more susceptible to infection
  - Pain in arms or legs

ZYNTEGLO will not give you an HIV infection. Treatment with Zynteglo may cause a false-positive human immunodeficiency virus (HIV) test result by some commercial tests. If you need to have an HIV test, talk with your healthcare provider about the appropriate test to use.
These are not all the possible side effects of ZYNTEGLO. Call your doctor for medical advice about side effects. You may report side effects to the FDA at 1-800-FDA-1088.

General information about the safe and effective use of ZYNTEGLO.
It is important that you have regular check-ups with your healthcare provider, including at least annual blood tests, to detect any adverse effects and to confirm that ZYNTEGLO is still working.
Talk to your healthcare provider about any concerns. You can ask your healthcare provider for information about ZYNTEGLO that is written for healthcare professionals.
For more information, go to ZYNTEGLO.com or call 1-833-666-2583 for bluebird Patient Services (my bluebird support).
Manufactured for: bluebird bio, Inc., Somerville, Massachusetts 02145

This Patient Information has been approved by the U.S. Food and Drug Administration.
Issued: August 2022

PRINCIPAL DISPLAY PANEL - 20 mL Bag Patient Identifier Label

betibeglogene autotemcel
zynteglo™

Suspension for IV infusion
20 mL containing 2.0 to 20 x 10^6 cells/mL
(1.7 to 20 x 10^6 CD34+ cells/mL)

Confirm Patient Identifiers

Last Name: $LastName$

First Name: $First Name$

Date of Birth: $DOB$

bbb Patient ID: $bbb_PatientID$

COI ID: $bbb_COI_ID$

LOT: $LOT$

EXP: $Expiry$

Bag X of X

DIN $DIN1_DIN2$

U.S. Lic. # 2160

bluebirdbio®

Label P/N: XXXXXXX

PRINCIPAL DISPLAY PANEL - 20 mL Bag Label

betibeglogene autotemcel
zynteglo™

Suspension for IV infusion
20 mL containing 2.0 to 20 x 10^6 cells/mL
(1.7 to 20 x 10^6 CD34+ cells/mL)

For autologous use only. For intravenous use only. Rx only.

Contains genetically modified autologous hematopoietic stem cells
suspended in cryopreservation solution containing 5% DMSO.

Not evaluated for infectious substances.

Do not irradiate. Do not use an in-line blood filter or infusion pump.

See full prescribing information for dosage and administration.

See Lot Information Sheet for number of infusion bags and CD34+
cells per kg for this patient.

P/N: XXXXXXX
Label P/N: XXXXXXX

Manufactured for: bluebird bio, Inc.
Somerville, MA 02145

PRINCIPAL DISPLAY PANEL - 20 mL Bag Cassette Label

betibeglogene autotemcel
zynteglo™

Suspension for IV infusion
20 mL containing 2.0 to 20 x 10^6 cells/mL
(1.7 to 20 x 10^6 CD34+ cells/mL)

For autologous use only. For intravenous use only. Rx only.

Contains genetically modified autologous hematopoietic stem cells
suspended in cryopreservation solution containing 5% DMSO.

Keep infusion bag(s) in the metal cassette(s). Store in the vapor phase of
liquid nitrogen at ≤ -140°C until ready for thaw and administration. Once
thawed do not re-freeze.

See full prescribing information for dosage and administration.

Do not irradiate. Do not use an in-line blood filter or infusion pump.

Not evaluated for infectious substances. No preservatives.

See Lot Information Sheet for number of infusion bags and CD34+ cells
per kg for this patient.

Confirm Patient Identifiers

Last Name: $LastName$

First Name: $First Name$

Date of Birth: $DOB$

bbb Patient ID: $bbb_PatientID$

COI ID: $bbb_COI_ID$

DIN: $DIN1_DIN2$

LOT: $LOT$

EXP: $Expiry$

Bag X of X

U.S.Lic. # 2160

bluebirdbio®

P/N: XXXXXXX
Label P/N: XXXXXXX

Manufactured for: bluebird bio, Inc.
Somerville, MA 02145
1-800-999-6378
ZYNTEGLO.com